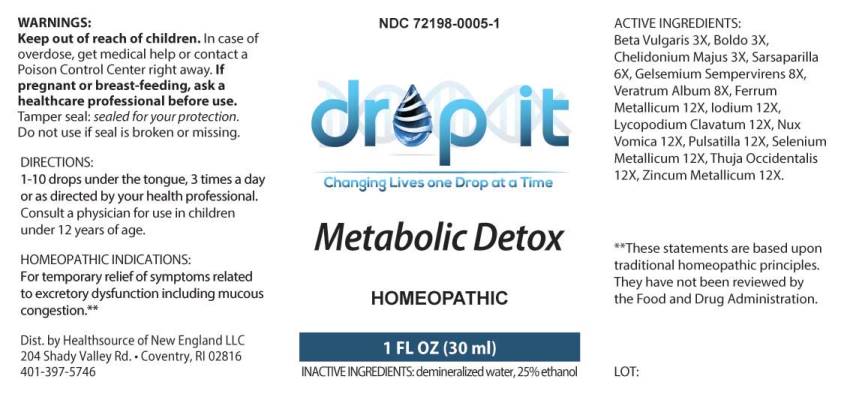 DRUG LABEL: Metabolic Detox
NDC: 72198-0005 | Form: LIQUID
Manufacturer: Healthsource of New England LLC
Category: homeopathic | Type: HUMAN OTC DRUG LABEL
Date: 20240122

ACTIVE INGREDIENTS: BETA VULGARIS WHOLE 3 [hp_X]/1 mL; PEUMUS BOLDUS LEAF 3 [hp_X]/1 mL; CHELIDONIUM MAJUS WHOLE 3 [hp_X]/1 mL; SMILAX ORNATA ROOT 6 [hp_X]/1 mL; GELSEMIUM SEMPERVIRENS ROOT 8 [hp_X]/1 mL; VERATRUM ALBUM ROOT 8 [hp_X]/1 mL; IRON 12 [hp_X]/1 mL; IODINE 12 [hp_X]/1 mL; LYCOPODIUM CLAVATUM SPORE 12 [hp_X]/1 mL; STRYCHNOS NUX-VOMICA SEED 12 [hp_X]/1 mL; PULSATILLA PRATENSIS WHOLE 12 [hp_X]/1 mL; SELENIUM 12 [hp_X]/1 mL; THUJA OCCIDENTALIS LEAFY TWIG 12 [hp_X]/1 mL; ZINC 12 [hp_X]/1 mL
INACTIVE INGREDIENTS: WATER; ALCOHOL

Drug Facts:

ACTIVE INGREDIENTS:

Beta Vulgaris 3X, Boldo 3X, Chelidonium Majus 3X, Sarsaparilla (Smilax Regelii) 6X, Gelsemium Sempervirens 8X, Veratrum Album 8X, Ferrum Metallicum 12X, Iodium 12X, Lycopodium Clavatum 12X, Nux Vomica 12X, Pulsatilla (Pratensis) 12X, Selenium Metallicum 12X, Thuja Occidentalis 12X, Zincum Metallicum 12X.

HOMEOPATHIC INDICATIONS:

For temporary relief of symptoms related to excretory dysfunction including mucous congestion.**

**These statements are based upon traditional homeopathic principles. They have not been reviewed by the Food and Drug Administration.

WARNINGS:

Keep out of reach of children. In case of overdose, get medical help or contact a Poison Control Center right away.

If pregnant or breast-feeding, ask a health professional before use.

Tamper seal: "Sealed for Your Protection." Do not use if seal is broken or missing.

Keep out of reach of children. In case of overdose, get medical help or contact a Poison Control Center right away.

DIRECTIONS:

1-10 drops under the tongue, 3 times a day or as directed by a health professional. Consult a physician for use in children under 12 years of age.

HOMEOPATHIC INDICATIONS:

For temporary relief of symptoms related to excretory dysfunction including mucous congestion.**

**These statements are based upon traditional homeopathic principles. They have not been reviewed by the Food and Drug Administration.

INACTIVE INGREDIENTS:

demineralized Water, 25% ethanol

QUESTIONS:

Dist. by Healthsource of New England LLC

204 Shady Valley Rd. • Coventry, RI 02816

401-397-5746

PACKAGE LABEL DISPLAY:

NDC 72198-0005-1

drop it

Changing Lives one Drop at a Time

Metabolic Detox

HOMEOPATHIC

1 FL OZ (30 ml)